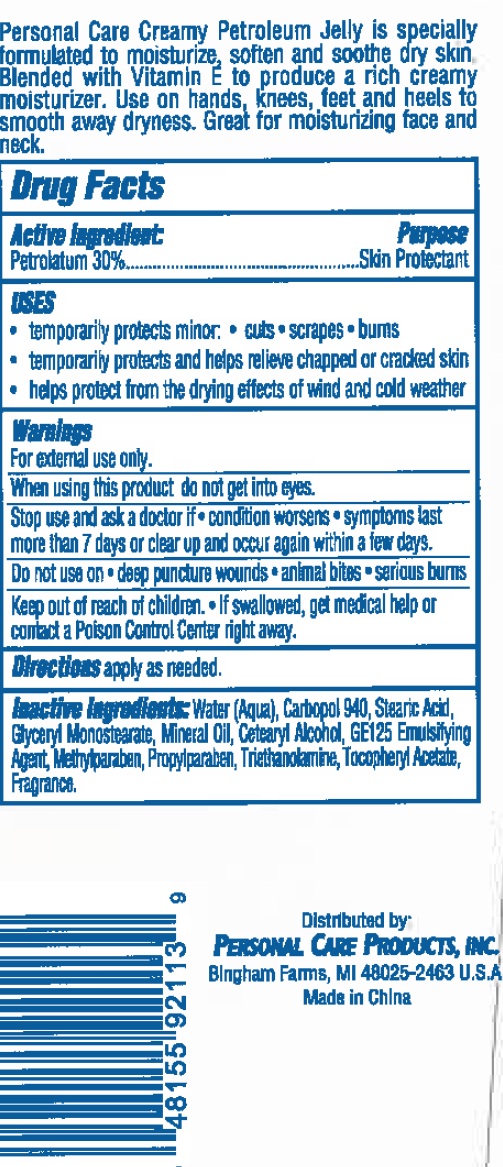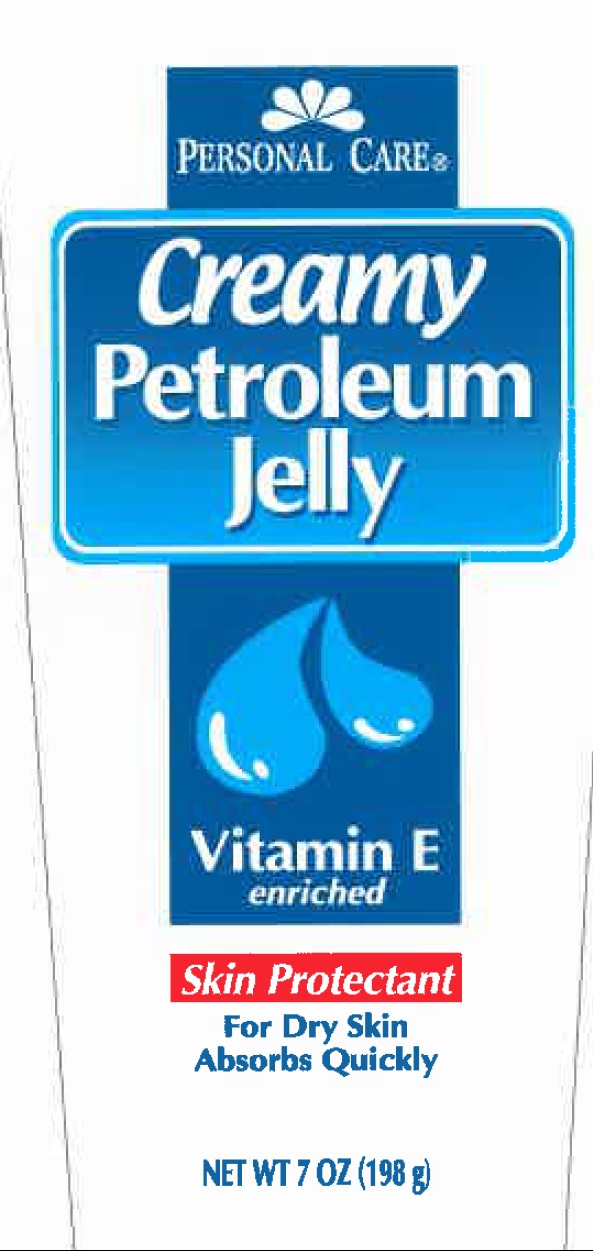 DRUG LABEL: Personal Care Creamy Petroleum Jelly
NDC: 29500-2113 | Form: CREAM
Manufacturer: PERSONAL CARE PRODUCTS, LLC
Category: otc | Type: HUMAN OTC DRUG LABEL
Date: 20110107

ACTIVE INGREDIENTS: PETROLATUM 30 g/100 g
INACTIVE INGREDIENTS: WATER; CARBOMER HOMOPOLYMER TYPE C; STEARIC ACID; GLYCERYL MONOSTEARATE; MINERAL OIL; CETOSTEARYL ALCOHOL; GLYCERYL MONOSTEARATE; METHYLPARABEN; PROPYLPARABEN; TROLAMINE; .ALPHA.-TOCOPHEROL ACETATE, D-

Personal Care Creamy Petroleum Jelly

Active Ingredient

Petrolatum 30%

Purpose

Skin Protectant

Uses

Temporarily protects minor: cuts, scrapes, burns

Temporarily protects and helps relieve chapped or cracked skin.

Helps protect from the drying effects of wind and cold weather.

Warnings

For external use only

When using this product do not get into eyes.

Stop use and ask a doctor if condition worsens, symptoms last more than 7 days or clear up and occur again within a few days.

Do not use on deep puncture wounds, animal bites, serious burns.

Keep out of reach of children. If swallowed, get medical help or contact a Poison Control Center right away.

DOSAGE AND ADMINISTRATION

Directions: apply as needed.

INACTIVE INGREDIENT

Inactive Ingredients: Water (aqua), carbopol 940, Stearic Acid, Glyceryl Monostearte, Mineral Oil, Cetearyl Alcohol, GE125 Emulsivying Agent, Methylparaben, Propylparaben, Triethanolamine, Tocopheryl Acetate, Fragrance.

PACKAGE LABEL

Personal Care

Creamy Petroleum Jelly

Vitamin E Enriched

Skin Protectant

For dry skin absorbs quickly

Personal Care Creamy Petroleum jelly is specially formulated to moisturize, soften and soothe dry skin. blended with Vitamin E to produce a rich creamy moisturizer. Use on hands, knees, feet and heels to smooth away dryness. Great for moisturizing face and neck.

Distributed by:

Personal Care Products, Inc.

Bingham Farms, MI 48025-2463 USA

Made in China